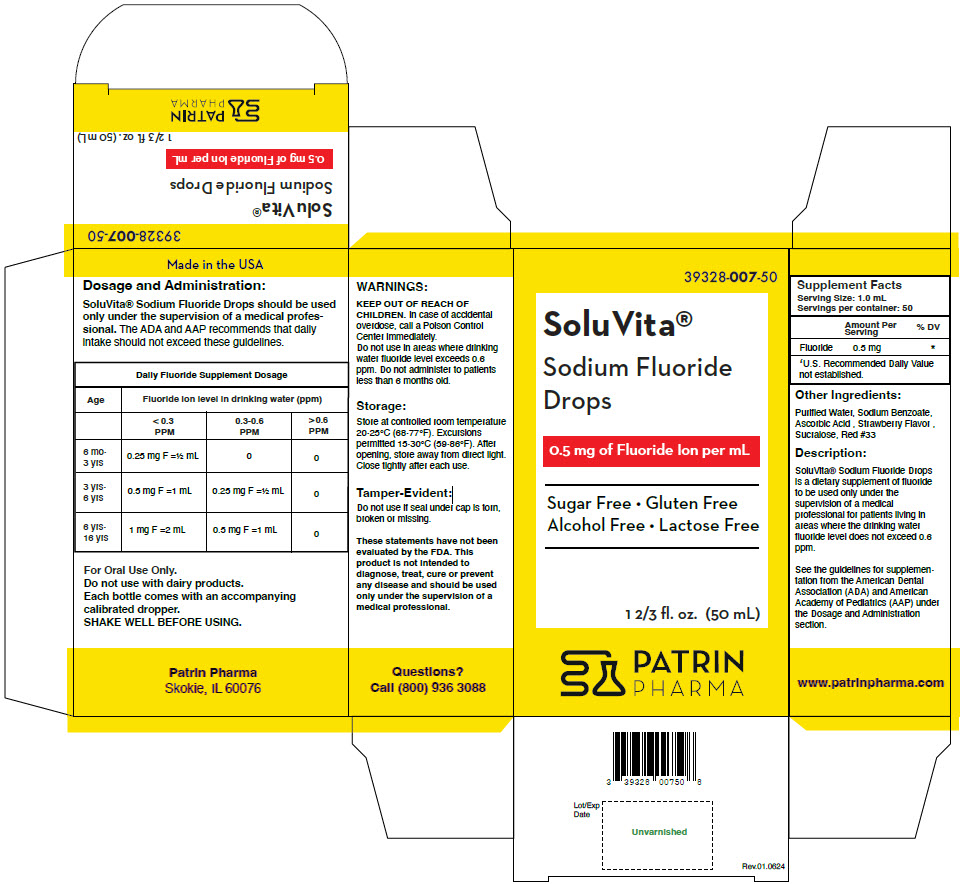 DRUG LABEL: SoluVita Sodium Fluoride Drops
NDC: 39328-007 | Form: LIQUID
Manufacturer: Patrin Pharma
Category: other | Type: DIETARY SUPPLEMENT
Date: 20250417

ACTIVE INGREDIENTS: Sodium Fluoride 0.5 mg/1 mL
INACTIVE INGREDIENTS: Water; Sodium benzoate; Ascorbic acid; STRAWBERRY; Sucralose; D&C RED NO. 33

SoluVita® Sodium Fluoride Drops

STATEMENT OF IDENTITY

Supplement Facts
Serving Size: 1.0 mL
Servings per container: 50
 | Amount Per Serving | % DV
Fluoride | 0.5 mg | [U.S. Recommended Daily Value not established.]

Other Ingredients

Purified Water, Sodium Benzoate, Ascorbic Acid , Strawberry Flavor , Sucralose, Red #33

Description

SoluVita® Sodium Fluoride Drops is a dietary supplement of fluoride to be used only under the supervision of a medical professional for patients living in areas where the drinking water fluoride level does not exceed 0.6 ppm.

See the guidelines for supplementation from the American Dental Association (ADA) and American Academy of Pediatrics (AAP) under the Dosage and Administration section.

WARNINGS

KEEP OUT OF REACH OF CHILDREN. In case of accidental overdose, call a Poison Control Center immediately.

Do not use in areas where drinking water fluoride level exceeds 0.6 ppm. Do not administer to patients less than 6 months old.

Storage

Store at controlled room temperature 20-25°C (68-77°F). Excursions permitted 15-30°C (59-86°F). After opening, store away from direct light. Close tightly after each use.

Tamper-Evident

Do not use if seal under cap is torn, broken or missing.

These statements have not been evaluated by the FDA. This product is not intended to diagnose, treat, cure or prevent any disease and should be used only under the supervision of a medical professional.

Questions?

Call (800) 936 3088

Dosage and Administration

SoluVita® Sodium Fluoride Drops should be used only under the supervision of a medical professional. The ADA and AAP recommends that daily intake should not exceed these guidelines.

Daily Fluoride Supplement Dosage
Age | Fluoride ion level in drinking water (ppm)
 | < 0.3 PPM | 0.3-0.6 PPM | > 0.6 PPM
6 mo-3 yrs | 0.25 mg F =½ mL | 0 | 0
3 yrs-6 yrs | 0.5 mg F =1 mL | 0.25 mg F =½ mL | 0
6 yrs-16 yrs | 1 mg F =2 mL | 0.5 mg F =1 mL | 0

For Oral Use Only.

Do not use with dairy products.

Each bottle comes with an accompanying calibrated dropper.

SHAKE WELL BEFORE USING.

HEALTH CLAIM

Made in the USA

Patrin Pharma
Skokie, IL 60076

www.patrinpharma.com

PRINCIPAL DISPLAY PANEL - 50 mL Bottle Carton

39328-007-50

SoluVita®
Sodium Fluoride
Drops

0.5 mg of Fluoride Ion per mL

Sugar Free • Gluten Free
Alcohol Free • Lactose Free

1 2/3 fl. oz. (50 mL)

PATRIN
PHARMA